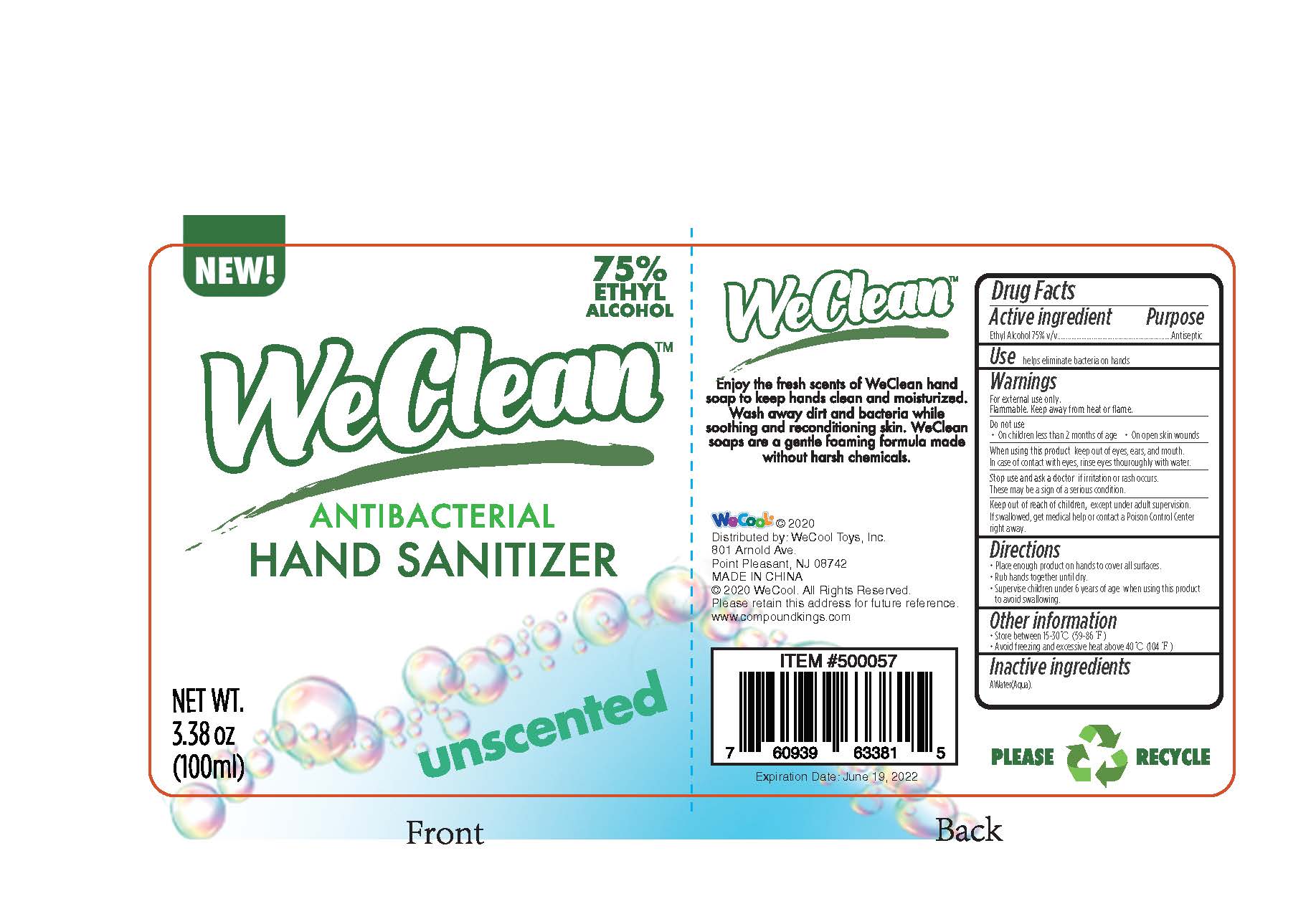 DRUG LABEL: WeClean Antibacterial Hand Sanitizer Unscented
NDC: 51706-921 | Form: LIQUID
Manufacturer: Landy International
Category: otc | Type: HUMAN OTC DRUG LABEL
Date: 20220321

ACTIVE INGREDIENTS: ALCOHOL 75 mL/100 mL
INACTIVE INGREDIENTS: WATER

51706-921 WeClean Antibacterial Hand Sanitizer Unscented Ethyl Alcohol(75%)

Active Ingredient(s)

Ethyl Alcohol (Vol.%)75%

Purpose

Antiseptic

Use

helps eliminate bacteria on hands

Warnings

For external use only.
Flammable, Keep away from heat or flame,
Do not use
On children less than 2 months of age. on open skin wounds
When using this product keep out of eyes, ear, and mouth.
In case of contact with eve, rinse eyes thouroughly with water
Stop use and ask a doctor if irritation or rash occurs,
These may be a sign of a serious condition.

Keep out of reach of children. except under adult supervision.

If swallowed, get medical help or contact a poison control center right away.

Directions

Place enough product on hands to cover all surfaces.

Rub hands together until dry.
Supervise children under 6 years of age When using this product to avoid swallowing.

Inactive ingredients

Water(Aqua)